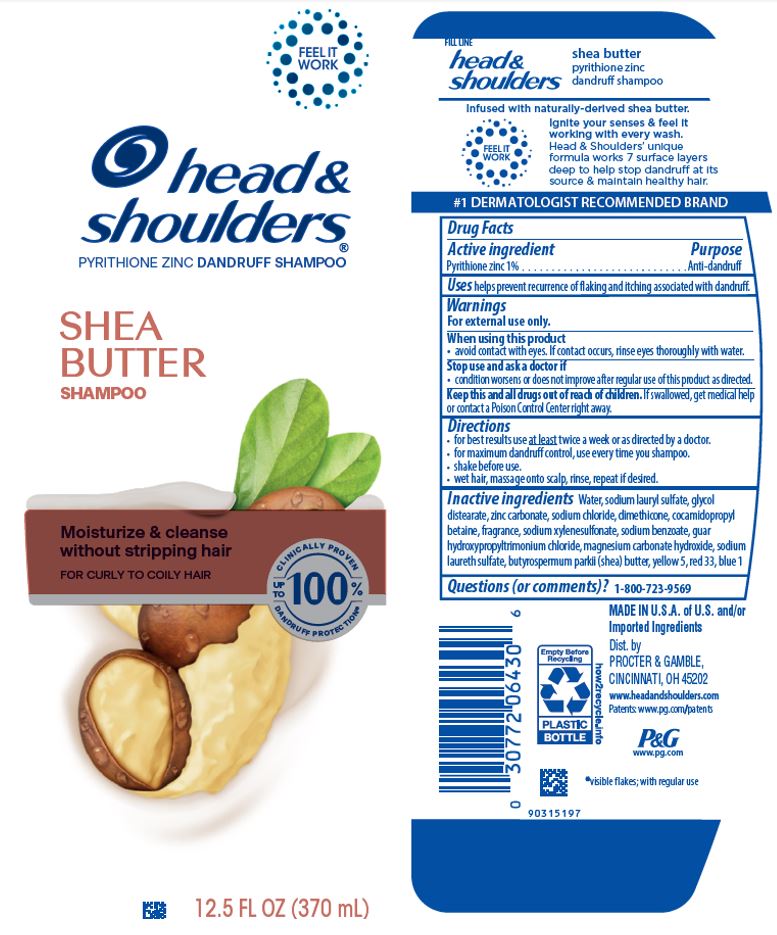 DRUG LABEL: Head and Shoulders Shea Butter Hair and Scalp Conditioner
NDC: 69423-669 | Form: OIL
Manufacturer: The Procter & Gamble Manufacturing Company
Category: otc | Type: HUMAN OTC DRUG LABEL
Date: 20251231

ACTIVE INGREDIENTS: PYRITHIONE ZINC 0.5 g/100 mL
INACTIVE INGREDIENTS: STEARAMIDOPROPYL DIMETHYLAMINE; WATER; STEARYL ALCOHOL; CETYL ALCOHOL; DIMETHICONE; PHENOXYETHANOL; BENZYL ALCOHOL; CITRIC ACID MONOHYDRATE; METHYLCHLOROISOTHIAZOLINONE; METHYLISOTHIAZOLINONE; SHEA BUTTER; FD&C YELLOW NO. 5; D&C RED NO. 33; FD&C BLUE NO. 1; GLUTAMIC ACID; SODIUM CHLORIDE

Head and Shoulders® Shea Butter Hair & Scalp Conditioner

Drug Facts

Active ingredient

Pyrithione zinc 0.5%

Purpose

Anti-dandruff

Uses

helps prevent recurrence of flaking and itching associated with dandruff.

Warnings

For external use only.

When using this product

- avoid contact with eyes. If contact occurs, rinse eyes thoroughly with water.

Stop use and ask a doctor if

- condition worsens or does not improve after regular use of this product as directed.

KEEP OUT OF REACH OF CHILDREN

Keep this and all drugs out of reach of children. If swallowed, get medical help or contact a Poison Control Center right away.

Directions

- for best results use at least twice a week or as directed by a doctor.
- apply to wet hair after shampooing by gently massaging into hair and scalp, rinse well.

Inactive ingredients

Water, stearyl alcohol, cetyl alcohol, stearamidopropyl dimethylamine, glutamic acid, dimethicone, fragrance, phenoxyethanol, benzyl alcohol, citric acid, sodium chloride, butyrospermumparkii(shea) butter, methylchloroisothiazolinone, methylisothiazolinone, yellow 5, red 33, blue 1

Questions (or comments)?

1-800-723-9569

Dist. by PROCTER & GAMBLE,
CINCINNATI, OH 45202

PRINCIPAL DISPLAY PANEL - 325 mL Tube Label

head &
shoulders
PYRITHIONE ZINC DANDRUFF CONDITIONER

SHEA BUTTER

HAIR & SCALP

CONDITIONER

Rich moisture

for scalp & hair

FOR CURLY TO COILY HAIR

10.9 FL OZ
(325 mL)